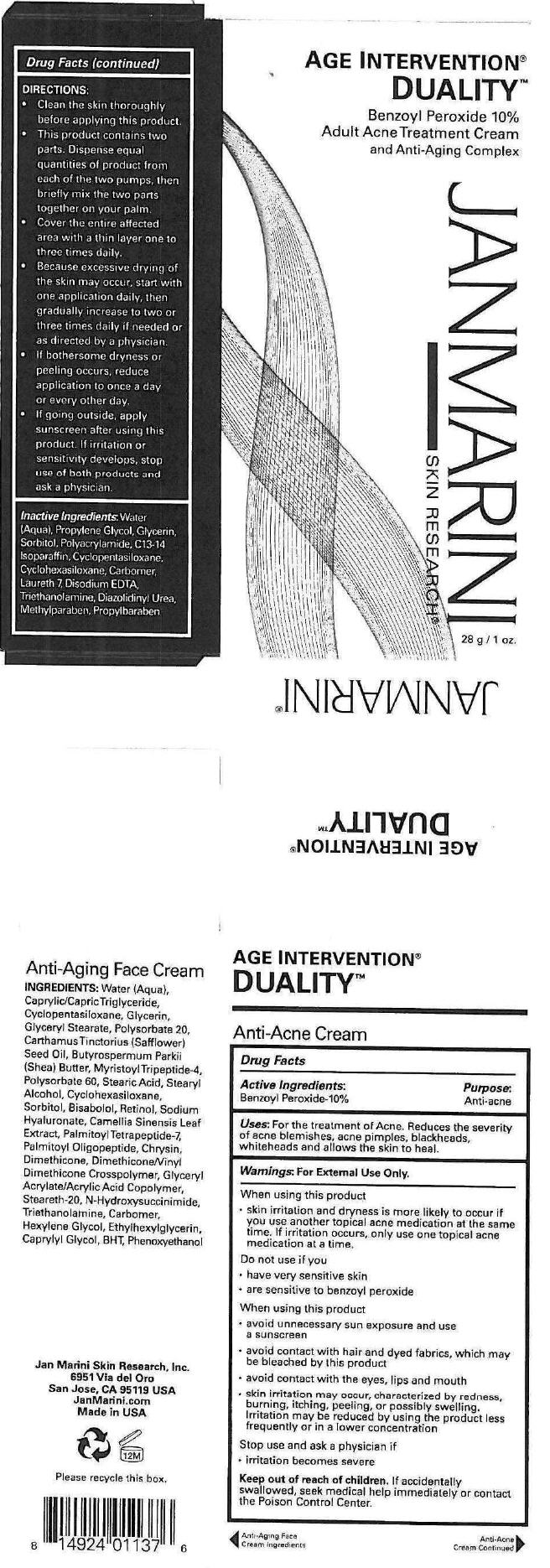 DRUG LABEL: AGE INTERVENTION DUALITY
NDC: 65113-2372 | Form: CREAM
Manufacturer: G.S. COSMECEUTICAL USA, INC.
Category: otc | Type: HUMAN OTC DRUG LABEL
Date: 20241115

ACTIVE INGREDIENTS: BENZOYL PEROXIDE 10 g/100 g
INACTIVE INGREDIENTS: WATER; GLYCERIN; GLYCERYL STEARATE CITRATE; POLYSORBATE 20; POLYSORBATE 60; STEARYL ALCOHOL; RETINOL; SORBITOL; CAMELLIA OLEIFERA LEAF; PALMITOYL TETRAPEPTIDE-7; PALMITOYL HEXAPEPTIDE-12; CHRYSIN; DIMETHICONE; STEARETH-20; PHENOXYETHANOL; HEXYLENE GLYCOL; ETHYLHEXYLGLYCERIN; CAPRYLYL GLYCOL

AGE INTERVENTION®
DUALITY™

Drug Facts

Active Ingredients

Benzoyl Peroxide-10%

Purpose

Anti-acne

Uses

For the treatment of Acne. Reduces the severity of acne blemishes, acne pimples, blackheads, whiteheads and allows the skin to heal.

Warnings

For External Use Only.

When using this product

- skin irritation and dryness is more likely to occur if you use another topical acne medication at the same time. If irritation occurs, only use one topical acne medication at a time.

Do not use if you

- have very sensitive skin
- are sensitive to benzoyl peroxide

When using this product

- avoid unnecessary sun exposure and use a sunscreen
- avoid contact with hair and dyed fabrics, which may be bleached by this product
- avoid contact with the eyes, lips and mouth
- skin irritation may occur, characterized by redness, burning, itching, peeling, or possibly swelling. Irritation may be reduced by using the product less frequently or in a lower concentration

Stop use and ask a physician if

- irritation becomes severe

Keep out of reach of children. If accidentally swallowed, seek medical help immediately or contact the Poison Control Center.

DIRECTIONS

- Clean the skin thoroughly before applying this product.
- This product contains two parts. Dispense equal quantities of product from each of the two pumps, then briefly mix the two parts together on your palm.
- Cover the entire affected area with a thin layer one to three times daily.
- Because excessive drying of the skin may occur, start with one application daily, then gradually increase to two or three times daily if needed or as directed by a physician.
- If bothersome dryness or peeling occurs, reduce application to once a day or every other day.
- If going outside, apply sunscreen after using this product. If irritation or sensitivity develops, stop use of both products and ask a physician.

Inactive Ingredients

Water (Aqua), Propylene Glycol, Glycerin, Sorbitol, Polyacrylamide, C13-14 Isoparaffin, Cyclopentasiloxane, Cyclohexasiloxane, Carbomer, Laureth 7, Disodium EDTA, Triethanolamine, Diazolidinyl Urea, Methylparaben, Propylbaraben

PRINCIPAL DISPLAY PANEL - 28 g Carton

AGE INTERVENTION®
DUALITY™

Benzoyl Peroxide 10%
Adult Acne Treatment Cream
and Anti-Aging Complex

JANMARINI
SKIN RESEARCH®

28 g / 1 oz.